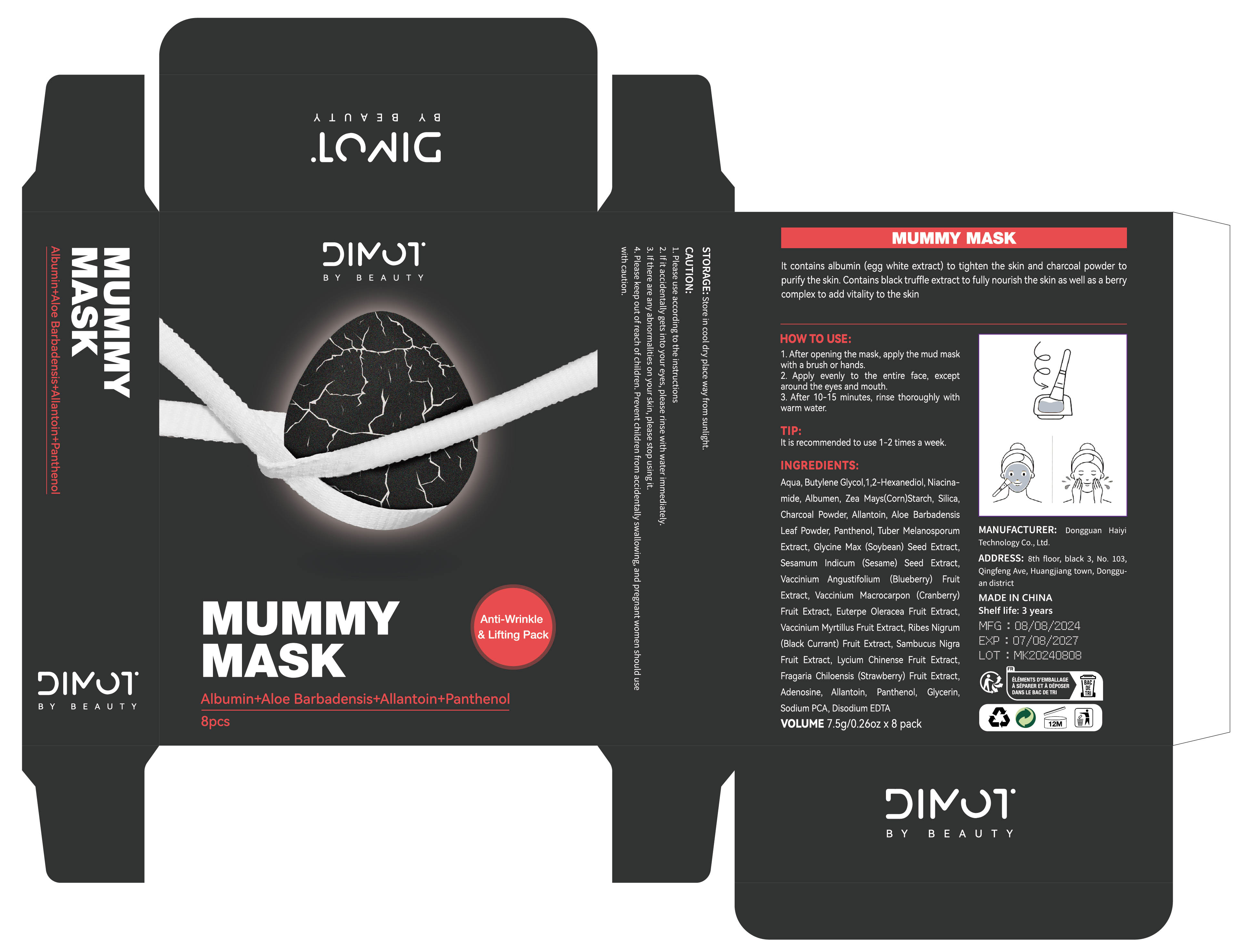 DRUG LABEL: MUMMY MASK
NDC: 84732-090 | Form: PASTE
Manufacturer: Dongguan Haiyi Technology Co.,Ltd.
Category: otc | Type: HUMAN OTC DRUG LABEL
Date: 20241109

ACTIVE INGREDIENTS: BUTYLENE GLYCOL 1 mg/100 g
INACTIVE INGREDIENTS: 1,2-HEXANEDIOL; ZEA MAYS (CORN) STARCH; SILICON DIOXIDE; ALOE BARBADENSIS LEAF POWDER; GLYCINE MAX (SOYBEAN) SEED EXTRACT; WATER; ALLANTOIN; PANTHENOL; CRANBERRY; CHARCOAL POWDER; TUBER MELANOSPORUM EXTRACT; SESAMUM INDICUM (SESAME) SEED EXTRACT; LOWBUSH BLUEBERRY; ALBUMEN; NIACINAMIDE

Active ingredient

Butylene Glycol

Inactive ingredient

Aqua, Butylene Glycol,1,2-Hexanediol, Niacina-mide, Albumen, Zea Mays(Corn)Starch, Silica,Charcoal Powder, Allantoin, Aloe BarbadensisLeaf Powder, Panthenol, Tuber MelanosporumExtract, Glycine Max (Soybean) Seed Extract,Sesamum Indicum(Sesame)Seed Extract,Vaccinium Angustifolium(Blueberry)FruitExtract, Vaccinium Macrocarpon(Cranberry)Fruit Extract, Euterpe Oleracea Fruit Extract,Vaccinium Myrtillus Fruit Extract, Ribes Nigrum(Black Currant) Fruit Extract, Sambucus NigraFruit Extract, Lycium Chinense Fruit Extract,Fragaria Chiloensis (Strawberry) Fruit Extract,Glycerin,Adenosine, Allantoin, Panthenol,Sodium PCA, Disodium EDTA

Purpose section

It contains albumin (egg white extract) to tighten the skin and charcoal powder topurify the skin. Contains black truffle extract to fully nourish the skin as well as a berrycomplex to add vitality to the skin

Warning

1.Please use according to the instructions
2. lf it accidentally gets into your eyes, please rinse with water immediately.
3. lf there are any abnormalities on your skin, please stop using it.
4. Please keep out of reach of children. Prevent children from accidentally swallowing, and pregnant women should usewith caution.

stop use

lf there are any abnormalities on your skin, please stop using it.

not use

Please keep out of reach of children, Prevent children from accidentally swallowing, and pregnant women should use
with caution.

OUT OF CHILDREN

Please keep out of reach of children

HOW TO USE

1.After opening the mask,apply the mud mask with a brush or hands.
2. Apply evenly to the entire face,except around the eyes and mouth.
3.After 10-i5 minutes, rinse thoroughly with warm wat

Dosage

It is recommended to use 1-2 times a week